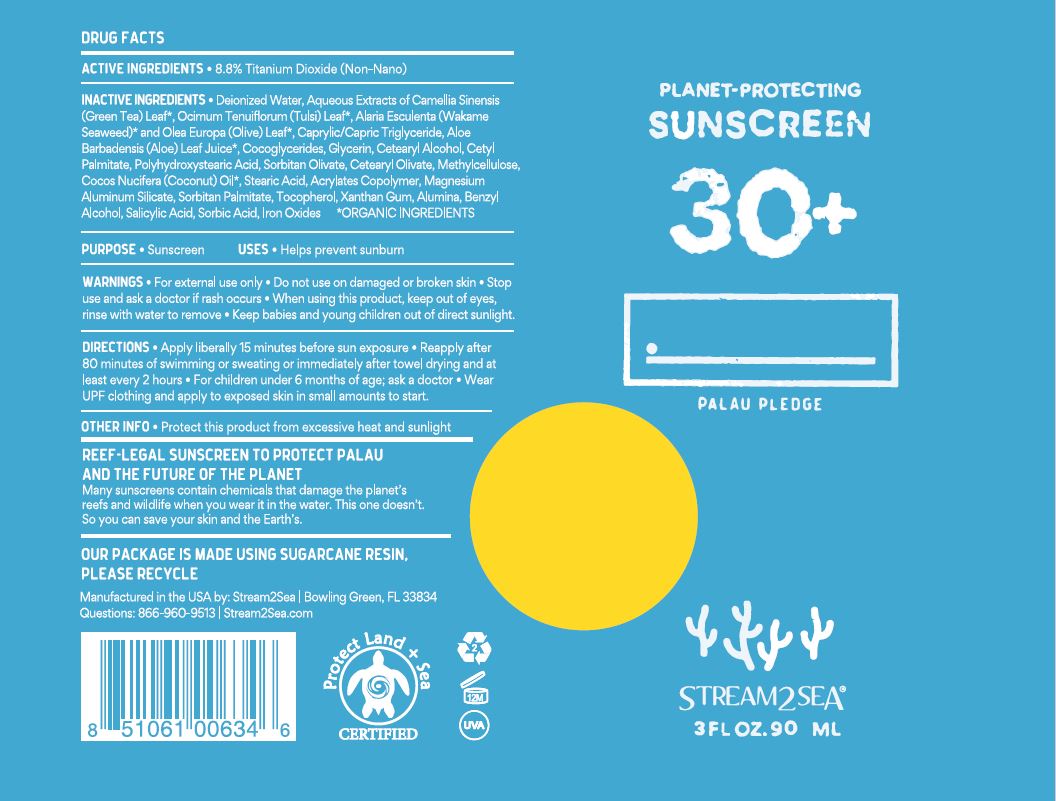 DRUG LABEL: Planet Protecting Sunscreen 30
NDC: 69555-037 | Form: LOTION
Manufacturer: Stream2Sea, LLC
Category: otc | Type: HUMAN OTC DRUG LABEL
Date: 20241221

ACTIVE INGREDIENTS: TITANIUM DIOXIDE 8.8 g/100 mL
INACTIVE INGREDIENTS: GREEN TEA LEAF; WATER; HOLY BASIL LEAF; ALARIA ESCULENTA; OLEA EUROPAEA LEAF; MEDIUM-CHAIN TRIGLYCERIDES; ALOE; COCO-GLYCERIDES; GLYCERIN; CETOSTEARYL ALCOHOL; CETYL PALMITATE; POLYHYDROXYSTEARIC ACID (2300 MW); SORBITAN OLIVATE; CETEARYL OLIVATE; METHYLCELLULOSE, UNSPECIFIED; COCONUT OIL; STEARIC ACID; METHACRYLIC ACID AND ETHYL ACRYLATE COPOLYMER; MAGNESIUM ALUMINUM SILICATE; SORBITAN MONOPALMITATE; TOCOPHEROL; XANTHAN GUM; BENZYL ALCOHOL; SALICYLIC ACID; SORBIC ACID; FERROUS OXIDE

Planet Protecting Sunscreen 30+

DRUG FACTS

ACTIVE INGREDIENTS

8.8% Titanium dioxide (Non-Nano)

PURPOSE
Sunscreen

USES

- Helps prevent sunburn

WARNINGS

- For external use only.
- Do not use on damaged or broken skin.
- Stop use and ask a doctor if rash occurs.
- When using this product, keep out of eyes, Rinse with water to remove.
- Keep babies and young children out of direct sunlight.

DIRECTIONS

- Apply liberally 15 minutes before sun exposure.
- Reapply after 80 minutes of swimming or sweating or immediately after towel drying and at least every 2 hours.
- For children under 6 months of age; ask a doctor.
- Wear UPF clothing and apply to exposed skin in small amounts to start.

OTHER INFORMATION

- Protect this product from excessive heat and sunlight
- REEF-LEGAL SUNSCREEN TO PROTECT PALAU AND THE FUTURE OF THE PLANET
  - Many sunscreens contain chemicals that damage the planet's reefs and wildlife when you wear it in the water. This one doesn't. So you can save your skin and the Earth's.

INACTIVE INGREDIENTS

Deionized Water, Aqueous Extracts of Camellia sinensis (Green Tea) Leaf*, Ocimum Tenuiflorum (Tulsi) Leaf*, Alaria Esculenta (Wakame Seaweed)* and Olea Europa (Olive) Leaf*, Caprylic/Capric Triglyceride, Aloe Barbedensis (Aloe) Leaf juice*, Cocoglycerides, Glycerin, Cetearyl Alcohol, Cetyl Palmitate, Polyhydroxystearic Acid, Sorbitan Olivate, Cetearyl Olivate, Methylcellulose, Cocos Nucifera (Coconut) Oil*, Stearic acid, Acrylates Copolymer, Magnesium Aluminium Silicate, Sorbitan Palmitate, Tocopherol, Xanthum Gum, Alumina, Benzyl Alcohol, Salicylic Acid, Sorbic Acid, Iron Oxides *ORGANIC INGREDIENTS

STORAGE AND HANDLING

OUR PACKAGE IS MADE USING SUGARCANE RESIN, PLEASE RECYCLE

Manufactured in the USA by: Stream2Sea | Bowling Green, FL 33834 Questions: 866-960-9513 | Stream2Sea.com

PACKAGE LABEL.PRINCIPAL DISPLAY PANEL

PLANET PROTECTING SUNSCREEN 30+ NDC 69555-037-30 - 3 FL OZ/90 ML - Label